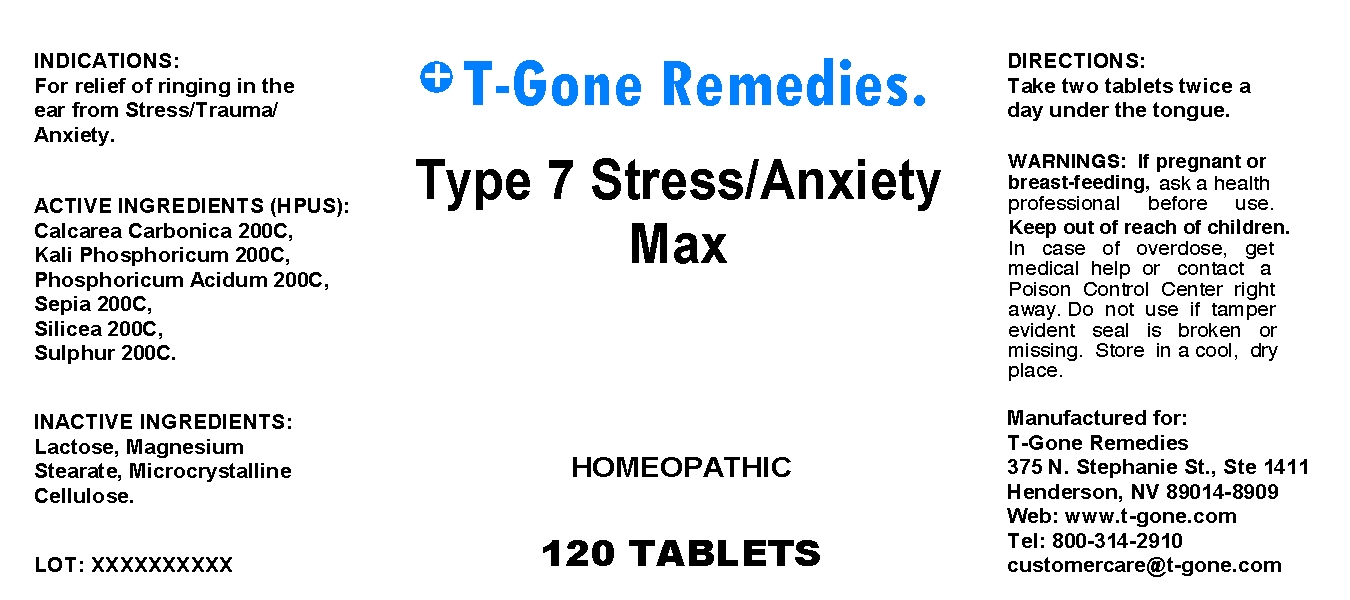 DRUG LABEL: Type 7 Stress Anxiety Max
NDC: 57520-0430 | Form: TABLET
Manufacturer: Apotheca Company
Category: homeopathic | Type: HUMAN OTC DRUG LABEL
Date: 20100715

ACTIVE INGREDIENTS: OYSTER SHELL CALCIUM CARBONATE, CRUDE 200 [hp_C]/1 mg; POTASSIUM PHOSPHATE, DIBASIC 200 [hp_C]/1 mg; PHOSPHORIC ACID 200 [hp_C]/1 mg; SEPIA OFFICINALIS JUICE 200 [hp_C]/1 mg; SULFUR 200 [hp_C]/1 mg
INACTIVE INGREDIENTS: LACTOSE; MAGNESIUM STEARATE; CELLULOSE, MICROCRYSTALLINE

Type 7 Stress Anxiety Max

ACTIVE INGREDIENT

ACTIVE INGREDIENTS: Calcarea carbonica 200C, Kali phosphoricum 200C, Phosphoricum acidum 200C, Sepia 200C, Silicea 200C, Sulphur 200C.

PURPOSE

INDICATIONS: For relief of ringing in the ear from Stress/Trauma/Anxiety.

WARNINGS

WARNINGS: If pregnant or breast-feeding, ask a health professional before use.

Keep out of reach of children. In case of overdose, get medical help or contact a Poison Control Center right away.

Do not use if tamper evident seal is broken or missing. Store in a cool, dry place.

DOSAGE AND ADMINISTRATION

DIRECTIONS: Take two tablets twice a day under the tongue.

INACTIVE INGREDIENT

INACTIVE INGREDIENTS: Lactose, Magnesium stearate, Microcrystalline cellulose.

QUESTIONS

Manufactured for:

T-Gone Remedies

375 N. Stephanie St., Ste 1411

Henderson, NV 89014-8909

Web: www.t-gone.com

Tel: 800-314-2910

customer care@t-gone.com

PACKAGE LABEL

T-Gone Remedies.

Type 7 Stress/Anxiety Max

HOMEOPATHIC

120 TABLETS